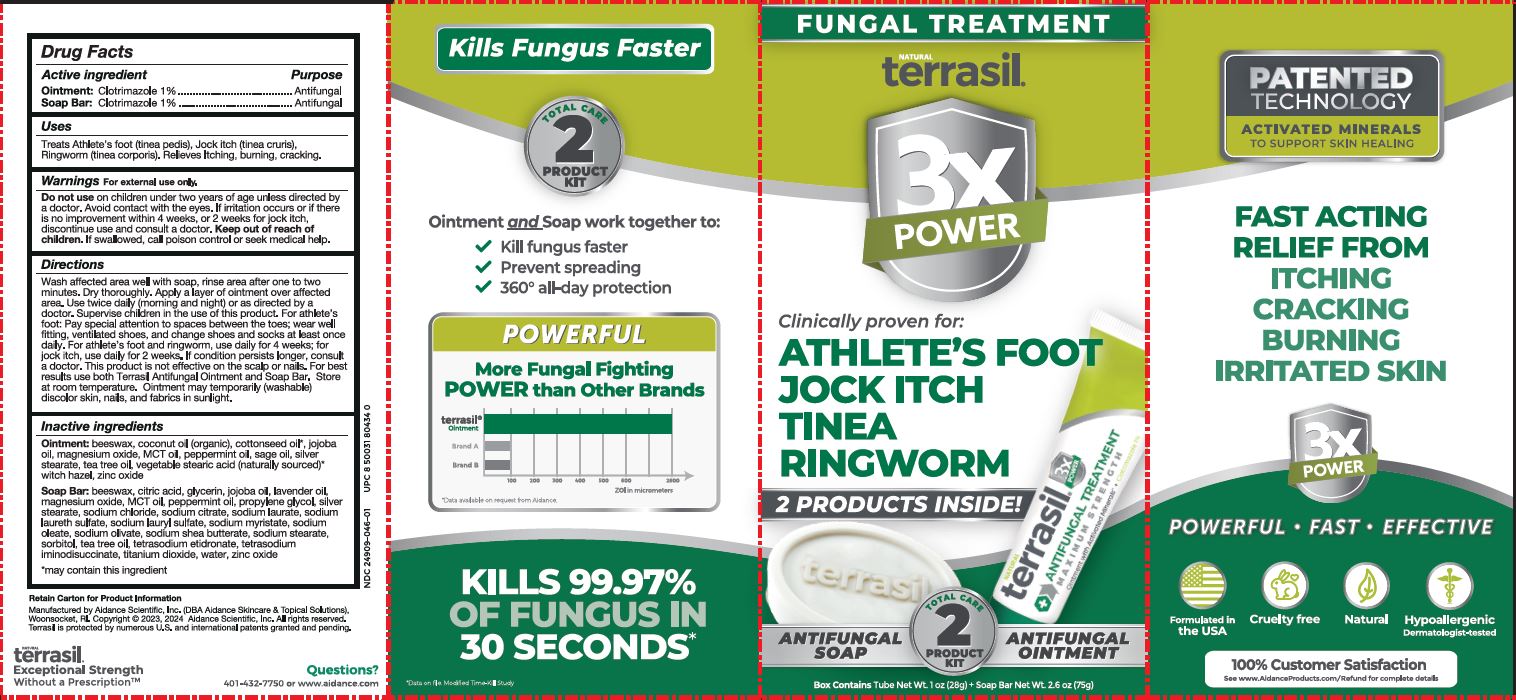 DRUG LABEL: terrasil Fungal Treatment
NDC: 24909-046 | Form: KIT | Route: TOPICAL
Manufacturer: Aidance Scientific, Inc., DBA Aidance Skincare & Topical Solutions
Category: otc | Type: HUMAN OTC DRUG LABEL
Date: 20241226

ACTIVE INGREDIENTS: CLOTRIMAZOLE 1 g/100 g; CLOTRIMAZOLE 1 g/100 g
INACTIVE INGREDIENTS: SODIUM CITRATE; SODIUM LAURATE; SODIUM LAURETH SULFATE; SODIUM MYRISTATE; SODIUM OLEATE; SODIUM OLIVATE; SODIUM STEARATE; TITANIUM DIOXIDE; CITRIC ACID MONOHYDRATE; PROPYLENE GLYCOL; PEPPERMINT OIL; TEA TREE OIL; ETIDRONATE TETRASODIUM; SILVER STEARATE; MAGNESIUM OXIDE; SODIUM CHLORIDE; SODIUM LAURYL SULFATE; SHEA BUTTER; WATER; ZINC OXIDE; TETRASODIUM IMINODISUCCINATE; YELLOW WAX; MEDIUM-CHAIN TRIGLYCERIDES; SORBITOL; JOJOBA OIL; GLYCERIN; LAVENDER OIL; PEPPERMINT OIL; MAGNESIUM OXIDE; PALM OIL; COTTONSEED OIL; SILVER STEARATE; COCONUT OIL; STEARIC ACID; JOJOBA OIL; SAGE OIL; WITCH HAZEL; YELLOW WAX; ZINC OXIDE; TEA TREE OIL

24909-046 terrasil Fungal Treatment

Active ingredients

Ointment: Clotrimazole 1%

Soap Bar: Clotrimazole 1%

Purpose

Antifungal

Uses

Treats Athlete’s foot (tinea pedis), Jock itch (tinea cruris),
Ringworm (tinea corporis). Relieves Itching, burning, cracking.

Warnings

For external use only.

Do not use on children under two years of age unless directed by a doctor. Avoid contact with the eyes. If irritation occurs or if there is no improvement within 4 weeks, or 2 weeks for jock itch, discontinue use and consult a doctor.

Keep out of reach of children.

OTHER SAFETY INFORMATION

If swallowed, get medical help or contact a Poison Control Center right away.

Directions

Wash affected area well with soap, rinse area after one to two minutes. Dry thoroughly. Apply a layer of ointment over affected area. Use twice daily (morning and night) or as directed by a doctor. Supervise children in the use of this product. For athlete’s foot: Pay special attention to spaces between the toes; wear well fitting, ventilated shoes, and change shoes and socks at least once daily. For athlete’s foot and ringworm, use daily for 4 weeks; for jock itch, use daily for 2 weeks. If condition persists longer, consult a doctor. This product is not effective on the scalp or nails. For best results use both Terrasil Antifungal Ointment and Soap Bar. Store at room temperature. Ointment may temporarily (washable) discolor skin, nails, and fabrics in sunlight.

Inactive ingredients

Ointment: beeswax, coconut oil (organic), cottonseed oil*, jojoba oil, magnesium oxide, MCT oil, peppermint oil, sage oil, silver stearate, tea tree oil, vegetable stearic acid (naturally sourced)* witch hazel, zinc oxide

Soap Bar: beeswax, citric acid, glycerin, jojoba oil, lavender oil, magnesium oxide, MCT oil, peppermint oil, propylene glycol, silver stearate, sodium chloride, sodium citrate, sodium laurate, sodium laureth sulfate, sodium lauryl sulfate, sodium myristate, sodium oleate, sodium olivate, sodium shea butterate, sodium stearate, sorbitol, tea tree oil, tetrasodium etidronate, tetrasodium iminodisuccinate, titanium dioxide, water, zinc oxide

*may contain this ingredient

Retain Carton for Product Information

Questions? 401-432-7750 or www.aidance.com